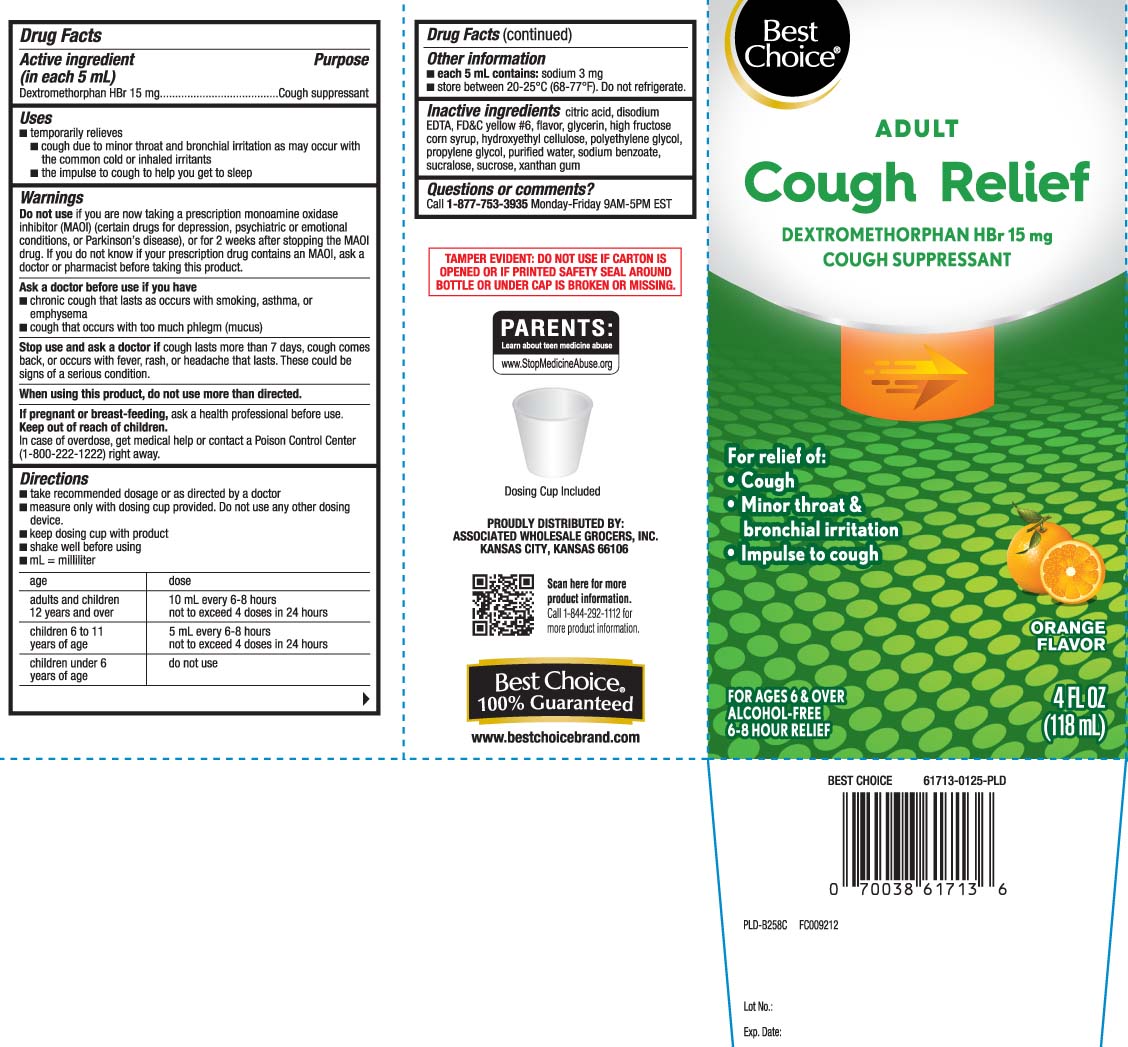 DRUG LABEL: Cough Relief
NDC: 63941-455 | Form: LIQUID
Manufacturer: Best Choice  (Valu Merchandisers Company)
Category: otc | Type: HUMAN OTC DRUG LABEL
Date: 20250116

ACTIVE INGREDIENTS: DEXTROMETHORPHAN HYDROBROMIDE 15 mg/5 mL
INACTIVE INGREDIENTS: ANHYDROUS CITRIC ACID; EDETATE DISODIUM; HYDROXYETHYL CELLULOSE (4000 MPA.S AT 1%); GLYCERIN; HIGH FRUCTOSE CORN SYRUP; POLYETHYLENE GLYCOL, UNSPECIFIED; PROPYLENE GLYCOL; WATER; SODIUM BENZOATE; SUCRALOSE; SUCROSE; XANTHAN GUM; FD&C YELLOW NO. 6

Drug Facts

Active ingredient (in each 5 mL)

Dextromethorphan HBr 15 mg

Purpose

Cough suppressant

Uses

- temporarily relieves
  - cough due to minor throat and bronchial irritation as may occur with the common cold or inhaled irritants
  - the impulse to cough to help you get to sleep

Warnings

Do not use

- if you are now taking a prescription monoamine oxidase inhibitor (MAOI) (certain drugs for depression, psychiatric or emotional conditions, or Parkinson's disease), or for 2 weeks after stopping the MAOI drug. If you do not know if your prescription drug contains an MAOI, ask a doctor or pharmacist before taking this product.

Ask a doctor before use if you have

- chronic cough that lasts as occurs with smoking, asthma or emphysema
- cough that occurs with too much phlegm (mucus)

Stop use and ask a doctor if

cough lasts more than 7 days, comes back, or is accompanied by fever, rash or headache that lasts. These could be signs of a serious condition.

When using this product

do not use more than directed

If pregnant or breast-feeding,

ask a health professional before use.

Keep out of reach of children.

In case of overdose, get medical help or contact a Poison Control Center (1-800-222-1222) right away.

Directions

- take recommended dosage or as directed by a doctor
- measure only with dosing cup provided. Do not use any other dosing device
- keep dosing cup with product
- shake well before using
- mL = milliliter

age | dose
adults and children 12 years and over | 10 mL every 6-8 hours not to exceed 4 doses in 24 hours
children 6 to under 11 years | 5 mL every 6-8 hours not to exceed 4 doses in 24 hours
children under 6 years | do not use

Other information

- each 5 mL contains: sodium 3 mg
- store between 20-25ºC (68-77ºF). Do not refrigerate

Inactive ingredients

citric acid, edetate disodium, FD&C yellow #6 flavor, glycerin, high fructose corn syrup, hydroxyethyl cellulose, polyethylene glycol, propylene glycol, purified water, sodium benzoate, sucralose, sucrose, xanthan gum

Questions or comments?

Call 1-877-753-3935 Monday-Friday 9AM-5PM EST

Principal Display Panel

ADULT

Cough Relief

DEXTROMETHORPHAN HBr 15 mg

COUGH SUPPRESSANT

For relief of:

- Cough
- Minor throat & bronchial irritation
- Impulse to cough

ORANGE FLAVOR

FOR AGES 6 & OVER

ALCOHOL-FREE

6-8 HOUR RELIEF

FL OZ (mL)

TAMPER EVIDENT: DO NOT USE IF CARTON IS OPENED OR IF PRINTED SAFETY SEAL AROUND BOTTLE OR UNDER CAP IS BROKEN OR MISSING.

PROUDLY DISTRIBUTED BY:

ASSOCIATED WHOLESALE GROCERS, INC.

KANSAS CITY, KANSAS 66106

Package Label

BEST CHOICE Adult Cough Relief Orange Flavor